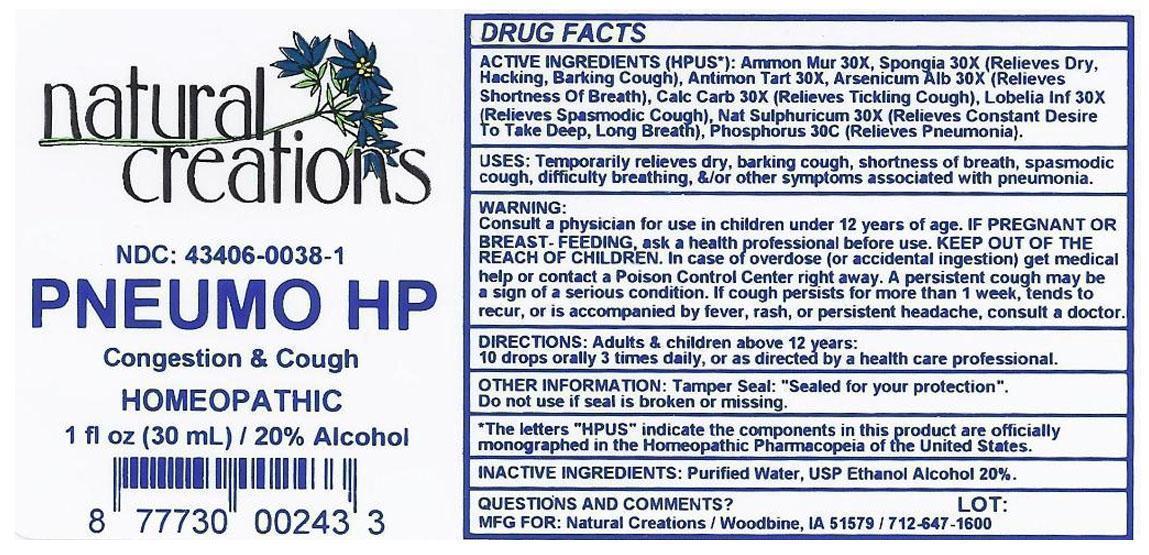 DRUG LABEL: PNEUMO HP
NDC: 43406-0038 | Form: LIQUID
Manufacturer: Natural Creations, Inc.
Category: homeopathic | Type: HUMAN OTC DRUG LABEL
Date: 20121112

ACTIVE INGREDIENTS: AMMONIUM CHLORIDE 30 [hp_X]/1 mL; ANTIMONY POTASSIUM TARTRATE 30 [hp_X]/1 mL; ARSENIC TRIOXIDE 30 [hp_X]/1 mL; OYSTER SHELL CALCIUM CARBONATE, CRUDE 30 [hp_X]/1 mL; LOBELIA INFLATA 30 [hp_X]/1 mL; SODIUM SULFATE 30 [hp_X]/1 mL; SPONGIA OFFICINALIS SKELETON, ROASTED 30 [hp_X]/1 mL; PHOSPHORUS 30 [hp_C]/1 mL
INACTIVE INGREDIENTS: WATER; ALCOHOL

PNEUMO HP

ACTIVE INGREDIENT

ACTIVE INGREDIENTS (HPUS*): Ammonium Muriaticum 30X, Antimonium Tartaricum 30X, Arsenicum Album 30X, Calcarea Carbonica 30C, Lobelia Inflata 30X, Natrum Sulphuricum 30X, Spongia Tosta 30X, Phosphorus 30C

INDICATIONS AND USAGE

USES: Temporarily relieves dry, barking cough, shortness of breath, spasmodic cough, difficulty breathing, &/or other symptoms associated with pneumonia.

WARNING:

Consult a physician for us in children under 12 years of age. IF PREGNANT OR BREAST-FEEDING, ask a health care professional before use. KEEP OUT OF THE REACH OF CHILDREN. In case of overdose (or accidental ingestion) get medical help or contact a Poison Control Center right away.

A persistent cough may be a sign of a serious condition. If cough persists for more than 1 week, tends to recur or is accompanied by fever, rash, or persistent headache, consult a doctor.

DOSAGE AND ADMINISTRATION

DIRECTIONS: Adults and children above 12 years: 10 drops orally 3 times daily, or as directed by a health care professional.

OTHER INFORMATION: Tamper Seal: "Sealed for your protection."

Do not use if seal is broken or missing.

REFERENCES

*The letters "HPUS" indicate the components in the product are officially monographed in the Homeopathic Pharmacopeia of the United States.

INACTIVE INGREDIENTS: Purified Water, USP Ethanol Alcohol 20%

QUESTIONS AND COMMENTS?

MFG FOR: Natural Creations / Woodbine, IA / 51579 712.647.1600

LOT:

PURPOSE

USES: Temporarily relieves dry, barking cough, shortness of breath, spasmodic cough, difficulty breathing, &/or symptoms associated with pneumonia.

KEEP OUT OF REACH OF CHILDREN

KEEP OUT OF THE REACH OF THE CHILDREN. In case of overdose (or accidental ingestion) get medical help or contact a Poison Control Center.

PACKAGE LABEL

NDC: 43406-0038-1

PNEUMO HP

Congestion & Cough

HOMEOPATHIC

1 fl oz (30 mL) / 20% Alcohol

UPC: 877730002433